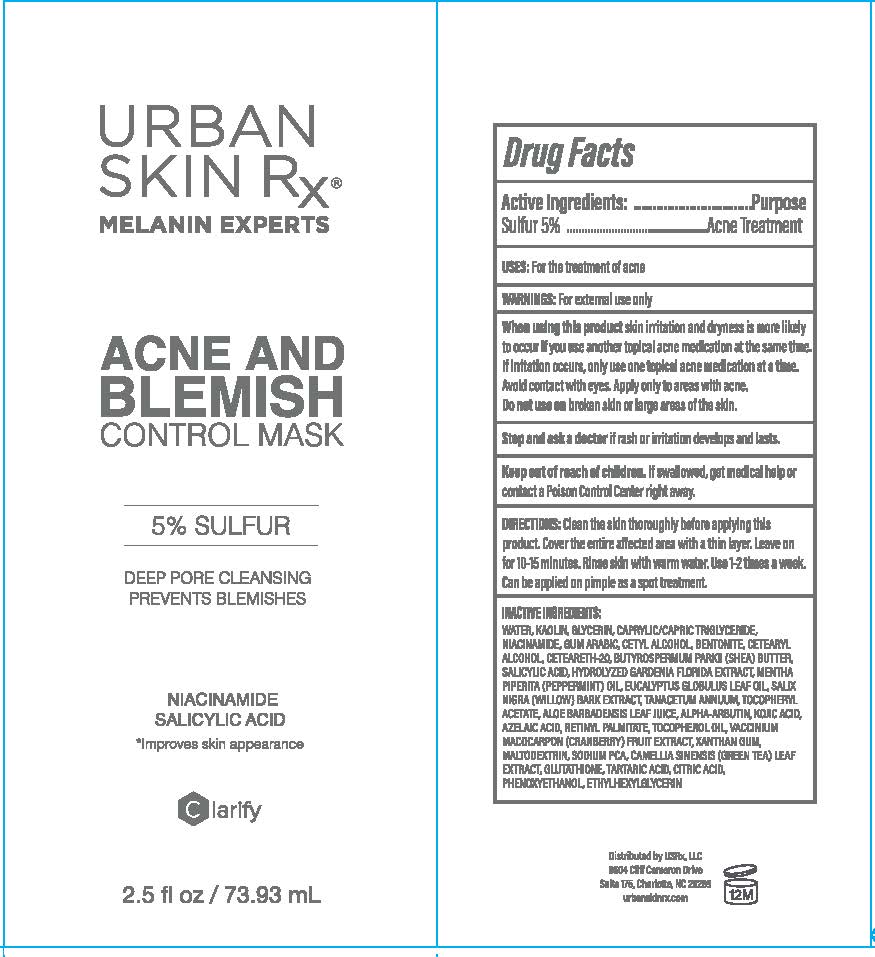 DRUG LABEL: ACNE AND BLEMISH CONTROL MASK
NDC: 70809-1906 | Form: CREAM
Manufacturer: USRX LLC
Category: otc | Type: HUMAN OTC DRUG LABEL
Date: 20241001

ACTIVE INGREDIENTS: SULFUR 5 g/100 mL
INACTIVE INGREDIENTS: SALICYLIC ACID; CETYL ALCOHOL; POLYOXYL 20 CETOSTEARYL ETHER; GARDENIA JASMINOIDES WHOLE; ACACIA; BENTONITE; CETOSTEARYL ALCOHOL; CRANBERRY JUICE; SODIUM PIDOLATE; CITRIC ACID MONOHYDRATE; PHENOXYETHANOL; PEPPERMINT OIL; AZELAIC ACID; MALTODEXTRIN; TARTARIC ACID; EUCALYPTUS OIL; GLUTATHIONE; NIACINAMIDE; MENTHA PIPERITA; SALIX NIGRA BARK; SHEA BUTTER; TOCOPHEROL; GLYCERIN; TANSY OIL; ETHYLHEXYLGLYCERIN; KAOLIN; ALOE VERA LEAF; ALPHA-TOCOPHEROL ACETATE; ALPHA-ARBUTIN; VITAMIN A PALMITATE; XANTHAN GUM; GREEN TEA LEAF; SODIUM PYRROLIDONE CARBOXYLATE; WATER; MEDIUM-CHAIN TRIGLYCERIDES; KOJIC ACID

Active ingredient

Sulfur 5%

Purpose

Acne Treatment

Uses:

For the treatment of acne

Warnings:

For external use only

When using this product

skin irritation and dryness is more likely to occur if you use another topical acne medication at the same time. If irriation occurs, only use one topical acne medication at a time. Avoid contact with eyes. Apply only to areas with acne. Do not use on broken skin or large areas of the skin.

Stop an dask a doctor

if rash or irritation develops and lasts.

Keep out of reach of children.

If swallowed, get medical help or contact a Poison Control Center right away.

Directions:

Clean the skin thoroguhly before applying this product. Cover the entire affected area with a thin layer. Leave on for 10-15 minutes. Rinse skin with warm water. Use 1-2 times a week. Can be applied on pimple as a spot treatment.

Inactive ingredients:

WATER, KAOLIN, GLYCERIN, CAPRYLIC/CAPRIC TRIGLYCERIDE, NIACINAMIDE, GUM ARABIC, CETYL ALCOHOL, BENTONITE, CETEARYL ALCOHOL, CETEARETH-20, BUTYROSPERMUM PARKII (SHEA) BUTTER, SALICYCLIC ACID, HYDROLYZED ARDENIA FLORIDA EXTRACT, MENTHA PIPERITA (PEPPERMINT) OIL, EUCALYPTUS GLOBULUS LEAF OIL, SALIX NIGRA (WILLOW) BARK EXTRACT, TANACETUM ANNUUM, TOCOPHERYL ACETATE, ALOE BARBADENSIS LEAF JUICE, ALPHA-ARBUTIN, KOJIC ACID, AZELAIC ACID, RETINYL PALMITATE, TOCOPHEROL OIL, VACCINIUM MACOCARPON (CRANBERRY) FRUIT EXTRACT, XANTHAN GUM, MALTODEXTRIN, SODIUM PCA, CAMELLIA SINENSIS (GREEN TEA) LEAF EXTRACT, GLUTATHIONE, TARTARIC ACID, CITRIC ACID, PHENOXYETHANOL, ETHYLHEXAYLGLYCERIN.